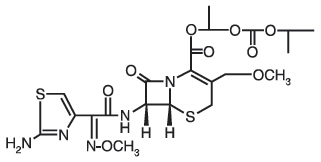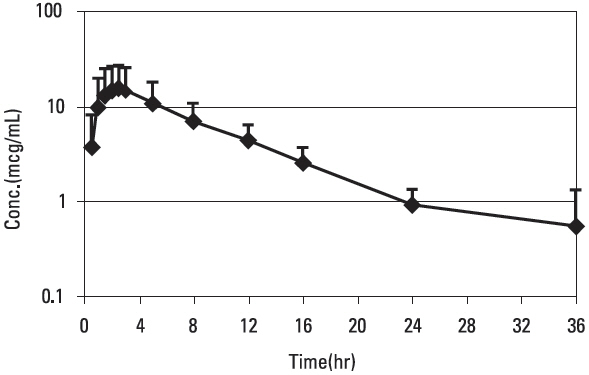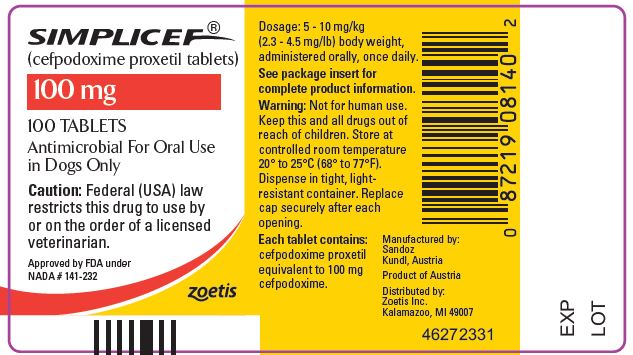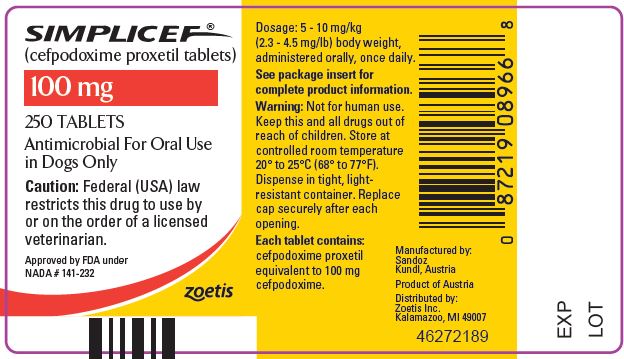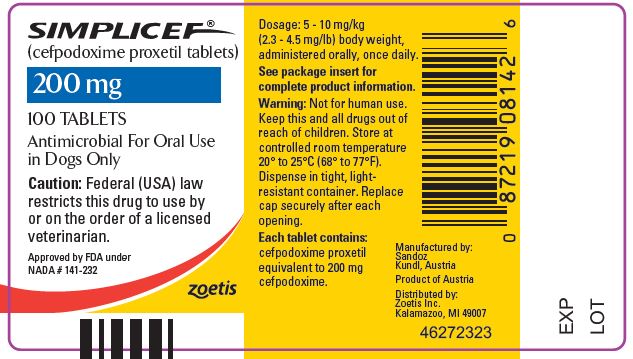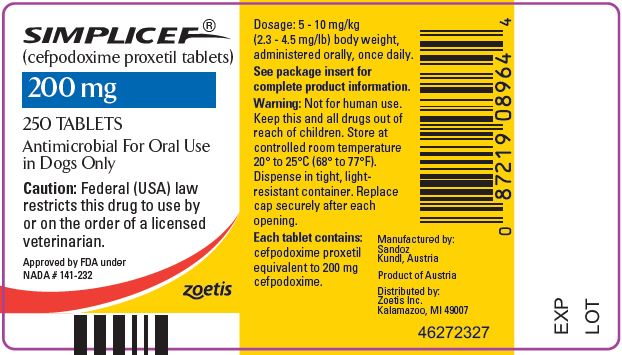 DRUG LABEL: Simplicef
NDC: 54771-5228 | Form: TABLET
Manufacturer: Zoetis Inc.
Category: animal | Type: PRESCRIPTION ANIMAL DRUG LABEL
Date: 20220914

ACTIVE INGREDIENTS: CEFPODOXIME PROXETIL 100 mg/1 1

SIMPLICEF®

SIMPLICEF®
(cefpodoxime proxetil tablets)

For Oral Use In Dogs Only

CAUTION

Federal (USA) law restricts this drug to use by or on the order of a licensed veterinarian.

DESCRIPTION

Cefpodoxime proxetil is an orally administered, extended spectrum, semi-synthetic cephalosporin antibiotic. The chemical name is: (+/-)-1-Hydroxyethyl(+)-(6R,7R)-7-[2-(2-amino-4-thiazolyl) glyoxylamido]-3-methoxymethyl)-8-oxo-5-thia-1-azabicyclo[4.2.0]oct-2-ene-2-carboxylate, 72-(Z)-(Omethyloxime), isopropyl carbonate (ester) [87239-81-4].

Cefpodoxime proxetil Chemical Structure:

Cefpodoxime proxetil is a prodrug; its active metabolite is cefpodoxime. All doses of SIMPLICEF (cefpodoxime proxetil) tablets are expressed in terms of the active cefpodoxime moiety. SIMPLICEF is available as:

100 mg Tablet, each reddish-orange, elliptical, scored tablet contains cefpodoxime proxetil equivalent to 100 mg of cefpodoxime.

200 mg Tablet, each light orange, round rectangle, scored tablet contains cefpodoxime proxetil equivalent to 200 mg of cefpodoxime.

INDICATION

SIMPLICEF tablets are indicated for the treatment of skin infections (wounds and abscesses) in dogs caused by susceptible strains of Staphylococcus intermedius, Staphylococcus aureus, Streptococcus canis (group G, β hemolytic), Escherichia coli, Pasteurella multocida, and Proteus mirabilis.

DOSAGE AND ADMINISTRATION

Dose range

The dose range of SIMPLICEF (cefpodoxime proxetil) tablets is 5-10 mg/kg (2.3-4.5 mg/lb) body weight, administered orally, once a day. The dose may be given with or without food. The determination of dosage for any particular patient must take into consideration such factors as the severity and nature of the infection, the susceptibility of the causative organisms, and the integrity of the patient's host-defense mechanisms. Obtain a sample of the pathogenic organism for culture and sensitivity testing prior to beginning antimicrobial therapy. Once results become available, continue with appropriate therapy.

Duration

SIMPLICEF tablets should be administered once daily for 5-7 days or for 2-3 days beyond the cessation of clinical signs, up to a maximum of 28 days. Treatment of acute infections should not be continued for more than 3-4 days if no response to therapy is seen.

Dosing Charts

For daily oral administration of SIMPLICEF at 5 mg/kg (Table 1) and 10 mg/kg (Table 2).

Table 1. Dose Table for SIMPLICEF Tablets at 5 mg/kg Total Daily Dosage
Weight of Dog (lbs)
Daily Dose |  | 22 | 44 | 66 | 88 | 132
No. of 100 mg tablets |  | 0.5 | 1 | 1.5 |  | 1
No. of 200 mg tablets |  |  |  |  | 1 | 1

Weight of Dog (kgs)
Daily Dose |  | 10 | 20 | 30 | 40 | 60
No. of 100 mg tablets |  | 0.5 | 1 | 1.5 |  | 1
No. of 200 mg tablets |  |  |  |  | 1 | 1

Table 2. Dose Table for SIMPLICEF Tablets at 10 mg/kg Total Daily Dosage
Weight of Dog (lbs)
Daily Dose | 11 | 22 | 44 | 66 | 88 | 132
No. of 100 mg tablets | 0.5 | 1 |  | 1
No. of 200 mg tablets |  |  | 1 | 1 | 2 | 3

Weight of Dog (kgs)
Daily Dose | 5 | 10 | 20 | 30 | 40 | 60
No. of 100 mg tablets | 0.5 | 1 |  | 1
No. of 200 mg tablets |  |  | 1 | 1 | 2 | 3

CONTRAINDICATIONS

Cefpodoxime proxetil is contraindicated in dogs with known allergy to cefpodoxime or to the β-lactam (penicillins and cephalosporins) group of antibiotics.

WARNINGS

Not for human use. Keep this and all drugs out of reach of children. Antimicrobial drugs, including penicillins and cephalosporins, can cause allergic reactions in sensitized individuals. To minimize the possibility of allergic reactions, those handling such antimicrobials, including cefpodoxime, are advised to avoid direct contact of the product with the skin and mucous membranes.

PRECAUTIONS

The safety of cefpodoxime proxetil in dogs used for breeding, pregnant dogs, or lactating bitches has not been demonstrated. As with other cephalosporins, cefpodoxime proxetil may occasionally induce a positive direct Coombs' test.

ADVERSE REACTIONS

A total of 216 dogs of various breeds and ages ranging from 2 months to 15 years were included in the field study safety analysis. The following table shows the number of dogs displaying each clinical observation.

Table 3. Abnormal Health Findings in the U.S. Field Study [Dogs may have experienced more than one of the observations during the study.]
Clinical Observation | SIMPLICEF (n=118) | Active Control (n=98)
Vomiting | 2 | 4
Diarrhea | 1 | 1
Increased water drinking | 0 | 2
Decreased appetite | 1 | 1

To report a suspected adverse reaction call 1-888-963-8471.

To request a safety data sheet (SDS) for SIMPLICEF tablets, call 1-888-963-8471.

CLINICAL PHARMACOLOGY

Pharmacokinetics/Pharmacodynamics

Cefpodoxime proxetil is a prodrug that is absorbed from and de-esterified in the gastrointestinal tract to its active metabolite, cefpodoxime. Following oral administration to fasting Beagles, oral bioavailability was 63.1 ± 5.3%.

Figure 1. Canine Plasma Concentration of Cefpodoxime After a Single Oral Dose of 10 mg/kg Cefpodoxime Proxetil Tablets

Cefpodoxime is distributed in the body with an apparent volume of distribution of 151 ± 27 mL/kg. Like other β-lactam antibiotics, cefpodoxime is eliminated from the body primarily in the urine, with an apparent elimination half-life of approximately 5-6 hours after oral administration. This is similar to the 4.7 hour apparent elimination half-life observed after intravenous dosing. Following intravenous administration of 10 mg/kg, the average total body clearance (ClB) was 22.7 ± 4.19 mL/hr/kg.

Table 4. Summary of Pharmacokinetic Parameters Obtained after a Single Oral Dose of 10 mg Cefpodoxime/kg BW, Administered as a Tablet
PK Parameter | Unit | Tablet (SD)
AUC0-∞ | mcg∙hr/mL | 145 (77.6)
AUC0-LOQ | mcg∙hr/mL | 142 (77.5)
Maximum concentration (Cmax) | mcg/mL | 16.4 (11.8)
Terminal plasma elimination half-life (t1/2,z) | hr | 5.61 (1.15)
Time of maximum concentration (tmax) | hr | 2.21 (0.542)
Mean residence time (MRT0-∞) | hr | 9.21 (1.97)

Microbiology

Like other β-lactam antibiotics, cefpodoxime exerts its inhibitory effect by interfering with bacterial cell wall synthesis. This interference is primarily due to its covalently binding to the penicillin-binding proteins (PBPs) (i.e. transpeptidase and/or carboxypeptidase), which are essential for synthesis of the bacterial cell wall. Therefore, cefpodoxime is bactericidal. Cefpodoxime is stable in the presence of many common β-lactamase enzymes. As a result, many organisms resistant to other β-lactam antibiotics (penicillins and some cephalosporins) due to the production of β-lactamases may be susceptible to cefpodoxime.

Cefpodoxime has a broad spectrum of clinically useful antibacterial activity that includes staphylococci, streptococci, and Gram-negative species (including Pasteurella, Escherichia, and Proteus). The compound is not active against most obligate anaerobes, Pseudomonas spp., or enterococci. The minimum inhibitory concentrations (MICs) for cefpodoxime against Gram-positive and Gram-negative pathogens isolated from canine skin infections (wounds and abscesses) in a 2002 U.S. field study are presented in Table 5. All MICs were determined in accordance with the National Committee for Clinical Laboratory Standards (NCCLS). Appropriate quality control (QC) ranges for in vitro susceptibility testing are presented in Table 6.

Table 5. Cefpodoxime Minimum Inhibitory Concentration Values (mcg/mL) from a 2002 Field Study Evaluating Skin Infections (wounds and abscesses) of Canines in the United States.
Organism [Veterinary specific interpretive criteria have not been established for the above listed canine pathogens by the NCCLS at this time.] | # of Isolates | MIC50 | MIC90 | Range
Staphylococcus intermedius | 118 | 0.12 | 0.50 | 0.12->32.0
Streptococcus canis (group G, β hemolytic) | 33 | ≤0.03 | ≤0.03 | ≤0.03 [No Range, all isolates yielded the same value.]
Escherichia coli | 41 | 0.25 | 0.50 | 0.12->32.0
Pasteurella multocida | 32 | ≤0.03 | ≤0.03 | ≤0.03-0.12
Proteus mirabilis | 14 | ≤0.03 | 0.06 | ≤0.03-0.06
Staphylococcus aureus | 19 | 2.0 | 2.0 | 0.12-2.0

Table 6. Acceptable Quality Control Ranges for Cefpodoxime
QC ATCC strain | KB Disk Diffusion Method |  | Broth Micro-dilution Method
 | Drug concentration | Zone diameter | MIC
Escherichia coli 25922 | 10 mcg | 23-28 mm [These ranges are for quality control strains used to monitor accuracy of minimum inhibitory concentrations (MICs) of non-fastidious organisms using cation-adjusted Mueller-Hinton agar or broth medium. The dilution range should encompass the QC ranges of these strains in the broth micro-dilution method.] | 0.25-1 mcg/mL
Staphylococcus aureus 25923 | 10 mcg | 19-25 mm
Staphylococcus aureus 29213 |  |  | 1-8 mcg/mL
Streptococcus pneumoniae 49619 | 10 mcg | 28-34 mm [These ranges are for quality control strains used to monitor accuracy of minimum inhibitory concentrations (MICs) of fastidious organisms. When susceptibility testing is performed for Streptococcus canis (group G, β hemolytic), Streptococcus pneumoniae ATCC 49619 should be included as a QC strain in the presence of 5% lysed sheep blood (KB disk diffusion method) or 2.5% lysed horse blood (broth micro-dilution method).] | 0.03-0.12 mcg/mL

EFFECTIVENESS

The clinical effectiveness of SIMPLICEF (cefpodoxime proxetil) was established in a multi-location (23 site) field study. In this study, 216 dogs with infected wounds or abscesses were treated with either SIMPLICEF (n=118) once daily at 5 mg/kg (2.3 mg/lb) body weight or with a active control antibiotic (n=98) administered twice daily for 5-7 days. In this study, SIMPLICEF was considered noninferior to the active control (88.7% versus 88.4% respectfully) in the treatment of canine skin infections (wounds and abscesses) caused by susceptible strains of Staphylococcus intermedius, Staphylococcus aureus, Streptococcus canis (group G, β hemolytic), Escherichia coli, Pasteurella multocida, and Proteus mirabilis.

ANIMAL SAFETY

In target animal safety studies, cefpodoxime was well tolerated at exaggerated daily oral doses of 100 mg/kg/day (10 times the maximum label dose) for 13 weeks in adult dogs and for 28 days in puppies (18- 23 days of age). Therefore, once daily administration of cefpodoxime oral tablets at the maximum labeled dose of 10 mg/kg for up to 28 days was shown to be safe in adult dogs and puppies.

Blood dyscrasia including neutropenias, may be seen following high doses of cephalosporins. Cephalosporin administration should be discontinued in such cases.

STORAGE INFORMATION

Store tablets at controlled room temperature 20° to 25°C (68° to 77°F). Dispense in tight, light-resistant container. Replace cap securely after each opening.

HOW SUPPLIED

SIMPLICEF tablets are available in the following strengths (cefpodoxime equivalent), colors, and sizes:
100 mg (reddish-orange, elliptical, scored, debossed with 5228)
Bottles of 100
Bottles of 250
200 mg (light orange, round rectangle, scored, debossed with 5229)
Bottles of 100
Bottles of 250

Approved by FDA under NADA # 141-232
zoetis
Manufactured by:
Sandoz
Kundl, Austria
Distributed by:
Zoetis Inc.
Kalamazoo, MI 49007
Revised: October 2020
46272333